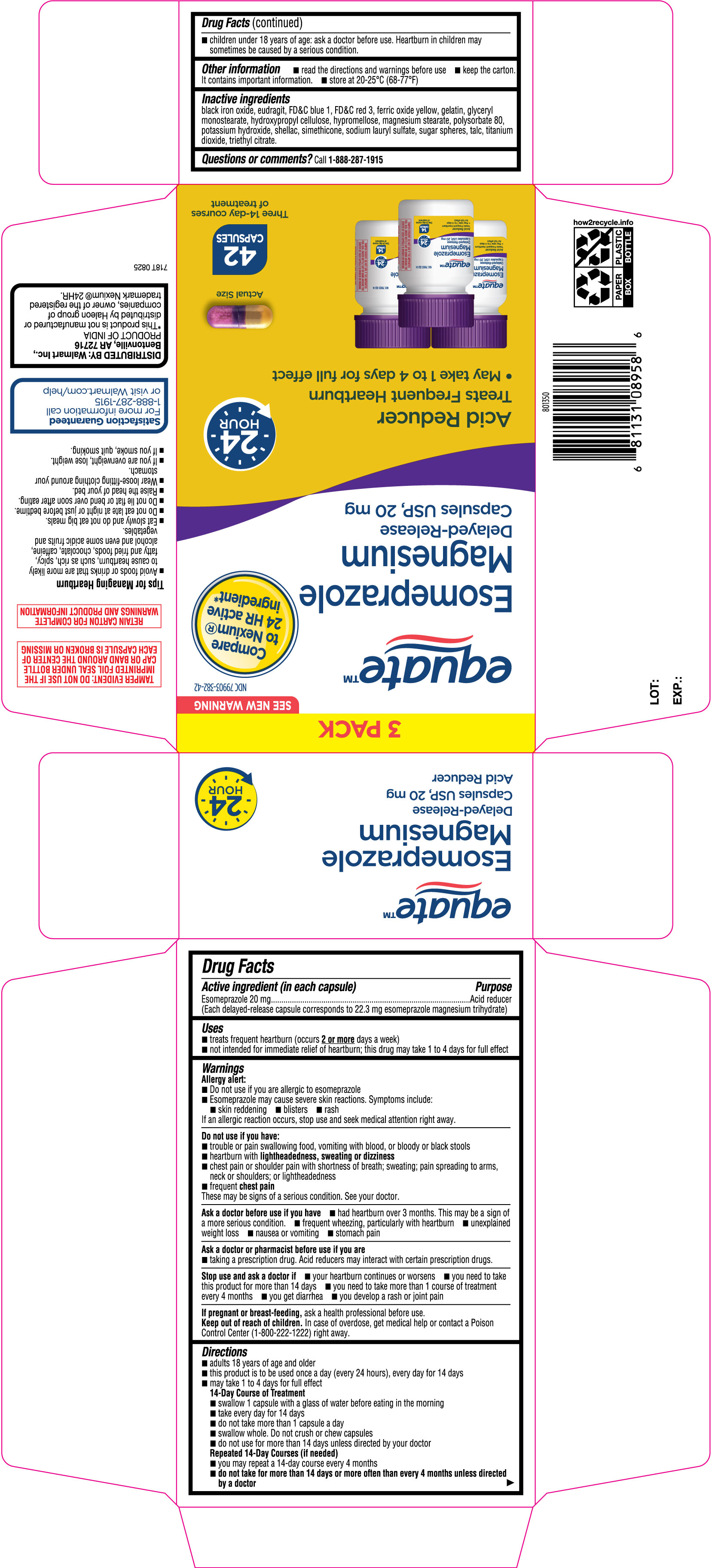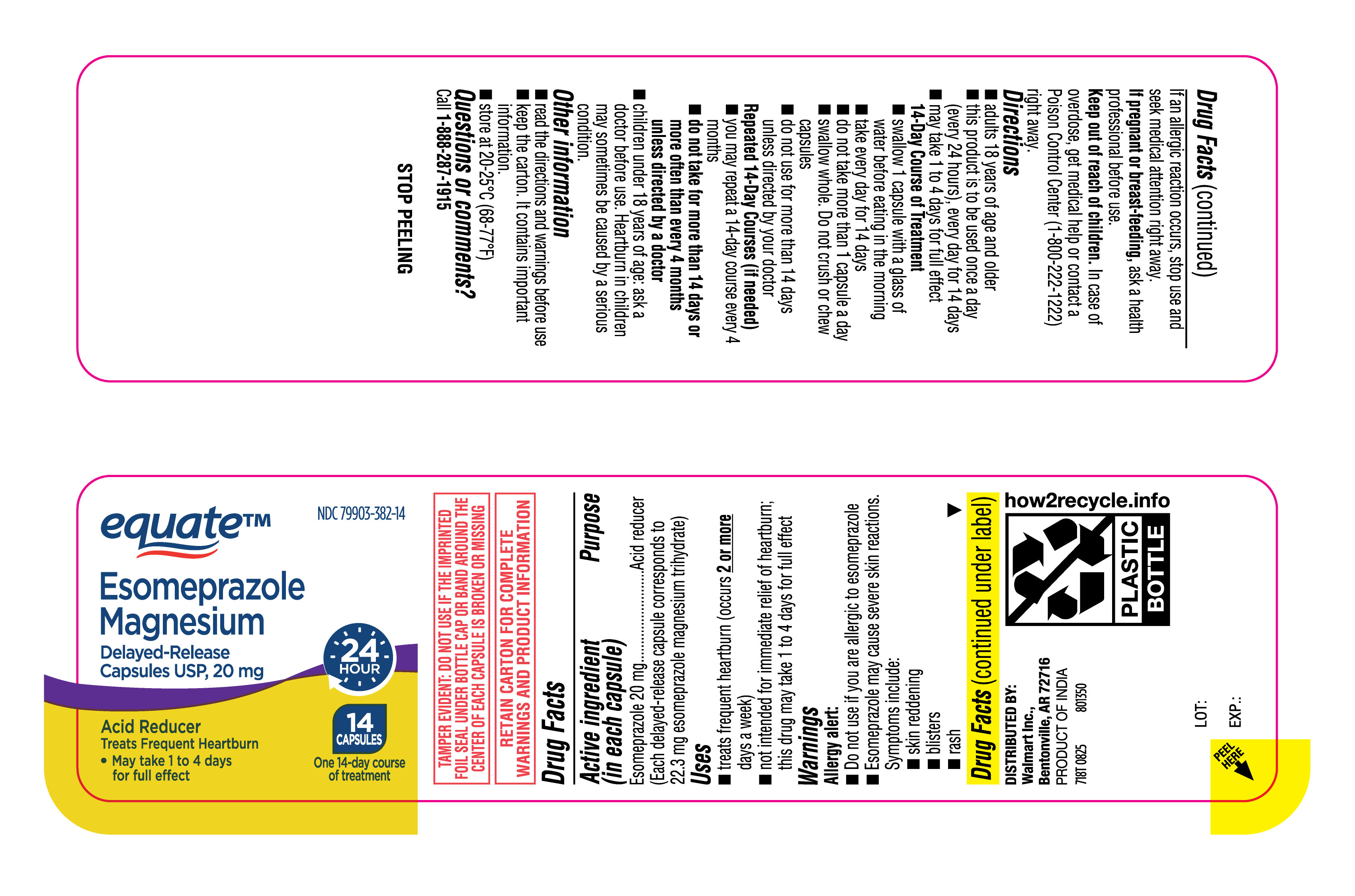 DRUG LABEL: Esomeprazole Magnesium
NDC: 79903-382 | Form: CAPSULE, DELAYED RELEASE
Manufacturer: Walmart Inc.
Category: otc | Type: HUMAN OTC DRUG LABEL
Date: 20250919

ACTIVE INGREDIENTS: ESOMEPRAZOLE MAGNESIUM 20 mg/1 1
INACTIVE INGREDIENTS: FD&C RED NO. 3; SHELLAC; DIMETHICONE; SUCROSE; TALC; FD&C BLUE NO. 1; GLYCERYL MONOSTEARATE; FERROSOFERRIC OXIDE; STARCH, CORN; TRIETHYL CITRATE; SODIUM LAURYL SULFATE; HYPROMELLOSE, UNSPECIFIED; FERRIC OXIDE YELLOW; MAGNESIUM STEARATE; METHACRYLIC ACID AND ETHYL ACRYLATE COPOLYMER; HYDROXYPROPYL CELLULOSE, UNSPECIFIED; POTASSIUM HYDROXIDE; GELATIN, UNSPECIFIED; TITANIUM DIOXIDE; POLYSORBATE 80

Walmart Esomeprazole Magnesium Delayed-Release Capsules USP, 20 mg

Drug Facts

Esomeprazole Magnesium Delayed-Release Capsules USP, 20 mg

Active ingredient (in each capsule)

Esomeprazole 20 mg

(Each delayed-release capsule corresponds to 22.3 mg esomeprazole magnesium trihydrate)

Purpose

Acid Reducer

Uses

- treats frequent heartburn (occurs 2 or more days a week)
- not intended for immediate relief of heartburn; this drug may take 1 to 4 days for full effect

Warnings

Allergy alert
• Do not use if you are allergic to esomeprazole
• Esomeprazole may cause severe skin reactions. Symptoms include:
o skin reddening
o blisters
o rash
If an allergic reaction occurs, stop use and seek medical attention right away.

Do not use if you have

• trouble or pain swallowing food, vomiting with blood, or bloody or black stools
• heartburn with lightheadedness, sweating or dizziness
• chest pain or shoulder pain with shortness of breath; sweating; pain spreading to arms, neck or shoulders; or lightheadedness
• frequent chest pain
These may be signs of a serious condition. See your doctor.

Ask a doctor before use if you have

- had heartburn over 3 months. This may be a sign of a more serious condition.
- frequent wheezing, particularly with heartburn
- unexplained weight loss
- nausea or vomiting
- stomach pain

Ask a doctor or pharmacist before use if you are

- taking a prescription drug. Acid reducers may interact with certain prescription drugs.

Stop use and ask a doctor if

- your heartburn continues or worsens
- you need to take this product for more than 14 days
- you need to take more than 1 course of treatment every 4 months
- you get diarrhea
- you develop a rash or joint pain

If pregnant or breast-feeding,

ask a health professional before use.

Keep out of reach of children.

In case of overdose, get medical help or contact a Poison Control Center (1-800-222-1222) right away.

Directions

• adults 18 years of age and older
• this product is to be used once a day (every 24 hours), every day for 14 days
• may take 1 to 4 days for full effect
14-Day Course of Treatment
o swallow 1 capsule with a glass of water before eating in the morning
o take every day for 14 days
o do not take more than 1 capsule a day
o swallow whole. Do not crush or chew capsules.
o do not use for more than 14 days unless directed by your doctor
Repeated 14-Day Courses (if needed)
o you may repeat a 14-day course every 4 months
o do not take for more than 14 days or more often than every 4 months unless directed by a doctor
• children under 18 years of age: ask a doctor before use. Heartburn in children may sometimes be caused by a serious condition.

Other information

- read the directions and warnings before use
- keep the carton. It contains important information.
- store at 20-25°C (68-77°F)

Inactive ingredients

black iron oxide, eudragit, FD&C blue 1, FD&C red 3, ferric oxide yellow, gelatin, glyceryl monostearate, hydroxypropyl cellulose, hypromellose, magnesium stearate, polysorbate 80, potassium hydroxide, shellac, simethicone, sodium lauryl sulfate, sugar spheres, talc, titanium dioxide, triethyl citrate

Questions or comments?

Call 1-888-287-1915

Tips for Managing Heartburn

• Avoid foods or drinks that are more likely to cause heartburn, such as rich, spicy, fatty and fried foods, chocolate, caffeine, alcohol and even some acidic fruits and vegetables.

• Eat slowly and do not eat big meals.

• Do not eat late at night or just before bedtime.

• Do not lie flat or bend over soon after eating.

• Raise the head of your bed.

• Wear loose-fitting clothing around your stomach.

• If you are overweight, lose weight.

• If you smoke, quit smoking.